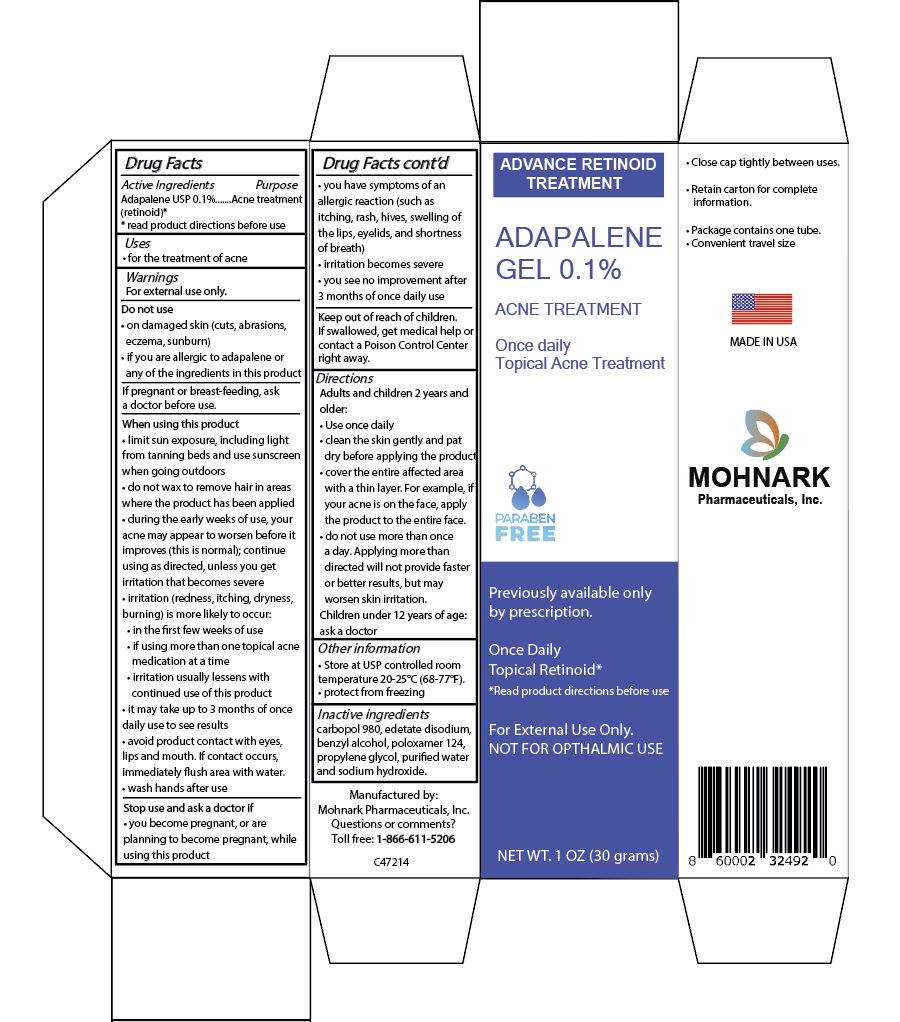 DRUG LABEL: Adapalene Gel 0.1%
NDC: 73715-003 | Form: GEL
Manufacturer: MOHNARK PHARMACEUTICALS INC
Category: otc | Type: HUMAN OTC DRUG LABEL
Date: 20250701

ACTIVE INGREDIENTS: ADAPALENE 0.1 g/100 g
INACTIVE INGREDIENTS: CARBOMER 980; BENZYL ALCOHOL; POLOXAMER 124; EDETATE DISODIUM; PROPYLENE GLYCOL; WATER; SODIUM HYDROXIDE

Adapalene Gel 0.1% Acne Treatment

ACTIVE INGREDIENT

Adapalene (retinoid) 0.1%

INACTIVE INGREDIENTS

Carbopol 980, edetate disodium, benzyl alcohol, Poloxamer 124, Propylene Glycol, Purified Water, Sodium Hydroxide

PURPOSE

Acne Treatment

WARNINGS

For external use only

USES

For the treatment of acne

DO NOT USE

- on damaged skin (cuts, abrasions, eczema, sunburn)
- If you are allergic to adapalene or any of the ingredients in this product

WHEN USING THIS PRODUCT

- limit sun exposure, including light from tanning beds and use sunscreen when going outdoors
- do not wax to remove hair in areas where the product has been applied
- during the early weeks of use, your acne may appear to worsen before it improves (this is normal); continue using as directed, unless you irritation that becomes severe
- irritation (redness, itching, dryness, burning) is more likely to occur
- in the first few weeks of use
- if using more more than one topical acne medication at a time
- but irritation usually lessens with continued use of this product
- it may take up to 3 months of once daily use to see results
- avoid product contact with eyes, lips and mouth. if contact occurs, immediately flush area with water
- wash hands after use

STOP USE AND ASK A DOCTOR IF

- you become pregnant, or are planning to become pregnant, while using this product
- you have symptoms of an allergic reaction (such as itching, rash, hives, swelling of the lips, eyelids and shortness of breath)
- irritation becomes severe
- you see no improvement after 3 months of once daily use

KEEP OUT OF REACH OF CHILDREN

If swallowed, get medical help or contact a Poison Control Center right away

DIRECTIONS

Adults and children 2 years and older:

- use once daily
- clean the skin gently and pat dry before applying the product
- cover the entire affected area with a thin layer. For example, if your acne is on the face, apply the product to the entire face
- do not use more than one time a day. Applying more than directed will not provide faster results or better results, but may worsen skin irritation.

Children under 12 years of age ask a doctor

OTHER INFORMATION

- Store at USP controlled room temperature 20 - 25^0 C (68 - 77^0F)
- protect from freezing

INDICATIONS AND USAGE

Adapalene is a topical retinoid used for treating acne vulgaris

RECENT MAJOR CHANGES

Added description for indications and usage

DOSAGE AND ADMINISTRATION

Apply a thin film of Adapalene Gel, 0.1% to the entire face and any other affected areas of the skin once daily in the evening, after washing gently with a non-medicated soap.

For topical use only. Not for ophthalmic, oral or intravaginal use.

PRINCIPAL DISPLAY PANEL

Carton Label - NDC 73715-003-01
Adapalene Gel, 0.1%

For external use only

Once daily Topical Acne Treatment

Net Wt 1 oz (30 grams)